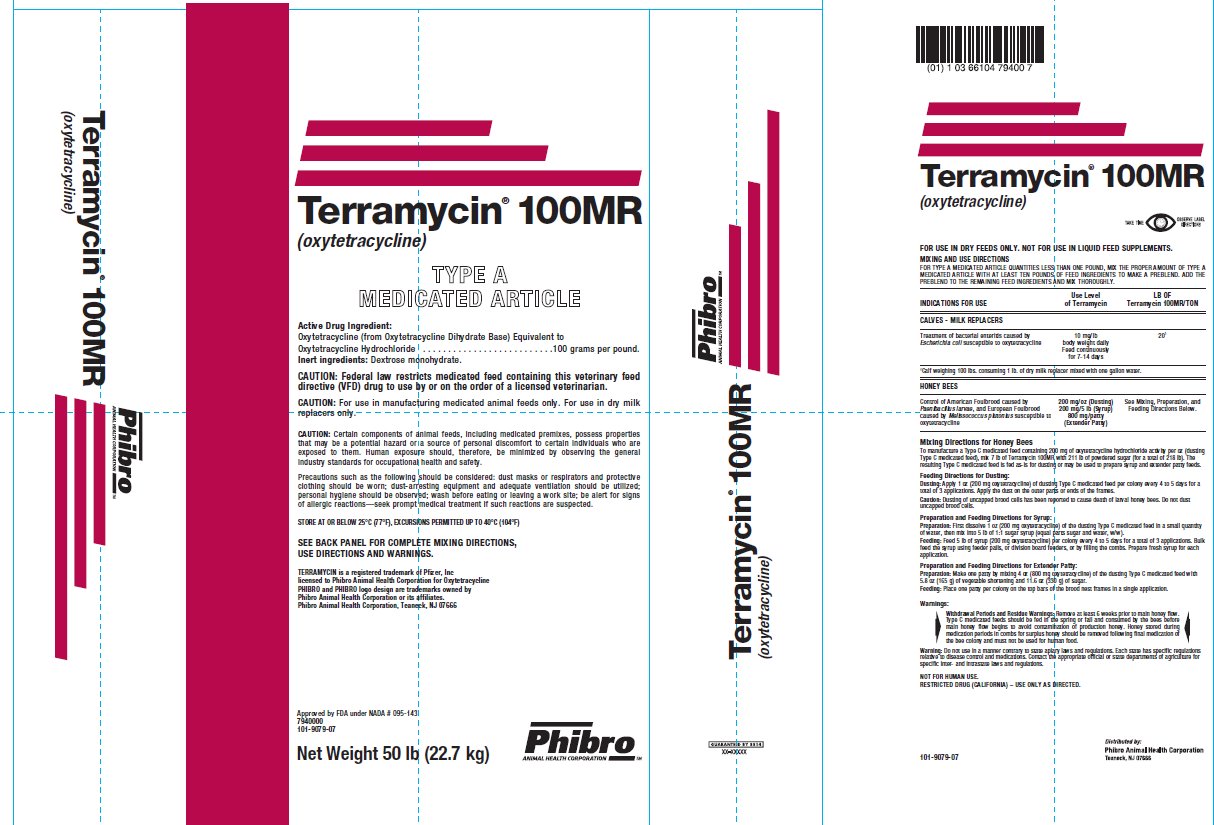 DRUG LABEL: Terramycin 100 MR
NDC: 66104-7940 | Form: POWDER
Manufacturer: Phibro Animal Health
Category: animal | Type: VFD TYPE A MEDICATED ARTICLE ANIMAL DRUG LABEL
Date: 20211207

ACTIVE INGREDIENTS: OXYTETRACYCLINE HYDROCHLORIDE 100 g/0.45 kg
INACTIVE INGREDIENTS: DEXTROSE, UNSPECIFIED FORM; SILICON DIOXIDE; POLYSORBATE 80

Terramycin® 100MR
(oxytetracycline)
TYPE A MEDICATED ARTICLE

Active Drug Ingredient:

Oxytetracycline (from Oxytetracycline Dihydrate Base) Equivalent to

Oxytetracycline Hydrochloride . . . . . . . . . . . . . . . . . . . . . . . . . .100 grams per pound.

Inert ingredients:

Dextrose monohydrate.

CAUTION: CAUTION: Federal law restricts medicated feed containing this veterinary feed directive (VFD) drug to use by or on the order of a licensed veterinarian.

CAUTION: For use in manufacturing medicated animal feeds only. For use in dry milk replacers only.

CAUTION: Certain components of animal feeds, including medicated premixes, possess properties that may be a potential hazard or a source of personal discomfort to certain individuals who are exposed to them. Human exposure should, therefore, be minimized by observing the general industry standards for occupational health and safety.

Precautions such as the following should be considered: dust masks or respirators and protective clothing should be worn; dust-arresting equipment and adequate ventilation should be utilized; personal hygiene should be observed; wash before eating or leaving a work site; be alert for signs of allergic reactions—seek prompt medical treatment if such reactions are suspected.

MIXING AND USE DIRECTIONS

FOR TYPE A MEDICATED ARTICLE QUANTITIES LESS THAN ONE POUND. MIX THE PROPER AMOUNT OF TYPE A MEDICATED ARTICLE WITH AT LEAST TEN POUNDS OF FEED INGREDIENTS TO MAKE A PREBLEND. ADD THE PREBLEND TO THE REMAINING FEED INGREDIENTS AND MIX THOROUGHLY.

INDICATIONS FOR USE | Use Level of Terramycin | LB OF Terramycin 100MR/TON
CALVES - MILK REPLACERS
Treatment of bacterial enteritis caused by Escherichia coli susceptible to oxytetracycline | 10 mg/lb body weight daily Feed continuously for 7-14 days | 20^1
^1Calf weighing 100 lbs. consuming 1 lb. of dry milk replacer mixed with one gallon water.
HONEY BEES
Control of American Foulbrood caused by Paenibacillus larvae, and European Foulbrood caused by Melissococcus plutonius susceptible to oxytetracycline | 200 mg/oz (Dusting); 200 mg/5 lb (Syrup); 800 mg/patty; (Extender Patty) | See Mixing, Preparation, and Feeding Directions below

Mixing and Use Directions for Honey Bees

To manufacture a Type C medicated feed containing 200 mg of oxytetracycline hydrochloride activity per oz (dusting Type C Medicated feed) mix 7 lb of Terramycin 100MR with 211 lb of powdered sugar (for a total of 218 lb). The resulting Type C medicated is fed as-is for dusting or may be used to prepare syrup and extender patty feeds.

Feeding Directions for Dusting:

Dusting: Apply 1 oz (200 mg oxytetracycline) of dusting Type C medicated feed per colony every 4 to 5 days for a total of 3 applications. Apply the dust on the outer parts or ends of the frames.

Caution: Dusting of uncapped brood cells has been reported to cause death of larval honey bees. Do not dust uncapped brood cells.

Preparation and Feeding Directions for Syrup:

Preparation: First dissolve 1 oz (200 mg oxytetracycline) of the dusting Type C medicated feed in a small quantity of water, then mix into 5 lb of 1:1 sugar syrup (equal parts sugar and water. w/w).

Feeding: Feed 5 lb of syrup (200 mg oxytetracycline) per colony every 4 to 5 days for a total of 3 applications. Bulk feed the syrup using feeder pails, or division board feeders, or by filling the combs. Prepare fresh syrup for each application.

Preparation and Feeding Directions for Extender Patty:

Preparation: Make one patty by mixing 4 oz (800 mg oxytetracycline) of the dusting Type C medicated with 5.8 oz. (165 g) of vegetable shortening and 11.6 oz (330 g) of sugar.

Feeding: Place one patty per colony on the top bars of the brood nest frames in a single application.

WARNING:

►Withdrawal Periods and Residue Warnings: Remove at least 6 weeks prior to main honey flow. Type C medicated feeds should be fed in the spring or fall and consumed by the bees before main honey begins to avoid contamination of production honey. Honey stored during medication periods in combs for surplus honey should be removed following final medication of the bee colony and must not be used for human food.

Warning: Do not use in a manner contrary to state apiary laws and regulations. Each state has specific regulations relative to disease control and medications. Contact the appropriate official or state departments of agriculture for specific inter- and intrastate laws and regulations.

NOT FOR HUMAN USE.

RESTRICTED DRUG (CALIFORNIA) – USE ONLY AS DIRECTED.

SEE BACK PANEL FOR COMPLETE MIXING DIRECTIONS,

USE DIRECTIONS AND WARNINGS.

Terramycin is a registered trademark of Pfizer, Inc.,

licensed to Phibro Animal Health Corporation for Oxytetracycline

PHIBRO and PHIBRO logo design are trademarks owned by

Phibro Animal Health Corporation or its affiliates.

Phibro Animal Health Corporation, Teaneck, NJ 07666

Approved by FDA under NADA #095-143

7940000

101-9079-07

Net Weight 50 lb (22.7 kg)